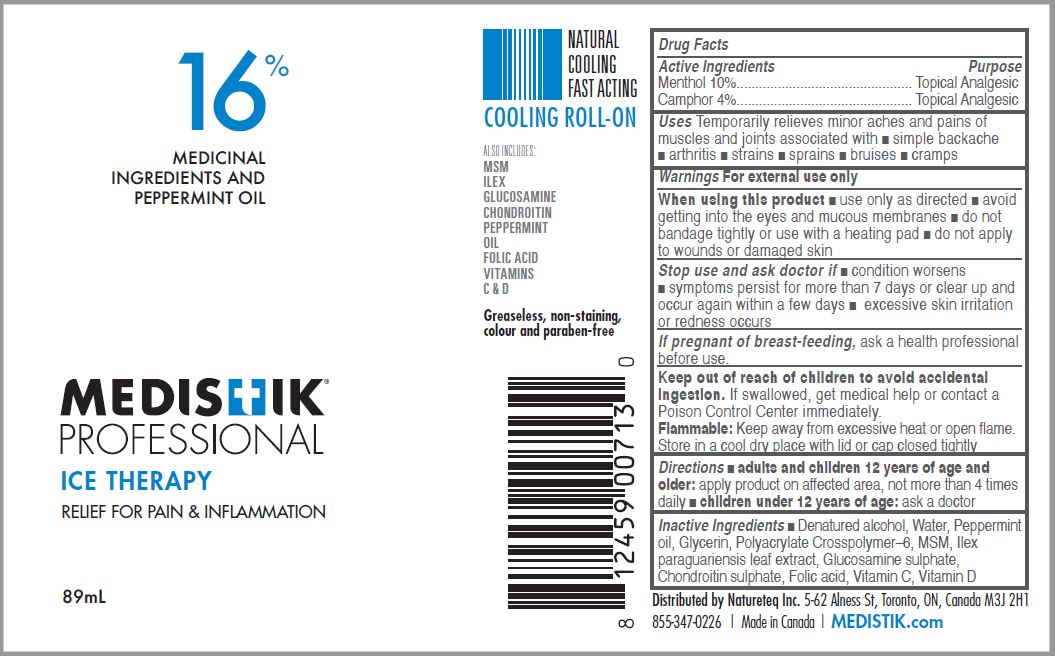 DRUG LABEL: MEDISTIK PROFESSIONAL ICE THERAPY
NDC: 50231-422 | Form: SOLUTION
Manufacturer: Natureteq Inc.
Category: otc | Type: HUMAN OTC DRUG LABEL
Date: 20240129

ACTIVE INGREDIENTS: MENTHOL 10 g/100 mL; CAMPHOR OIL 4 g/100 mL
INACTIVE INGREDIENTS: ILEX PARAGUARIENSIS LEAF; GLUCOSAMINE SULFATE; CHONDROITIN SULFATE (CHICKEN); FOLIC ACID; ASCORBIC ACID; VITAMIN D; ALCOHOL; WATER; PEPPERMINT OIL; GLYCERIN; AMMONIUM ACRYLOYLDIMETHYLTAURATE, DIMETHYLACRYLAMIDE, LAURYL METHACRYLATE AND LAURETH-4 METHACRYLATE COPOLYMER, TRIMETHYLOLPROPANE TRIACRYLATE CROSSLINKED (45000 MPA.S); DIMETHYL SULFONE

Natureteq (as PLD) - MEDISTIK PROFESSIONAL ICE THERAPY ROLL-ON (50231-422)

ACTIVE INGREDIENTS

Menthol 10%

Camphor 4%

PURPOSE

Topical Analgesic

USES

For the temporary relief of sore muscles and joints associated with

- simple backache
- arthritis
- strains
- sprains
- bruises
- cramps

WARNINGS

When using this product

- use only as directed
- avoid getting into the eyes and mucous membranes
- do not bandage tightly or use with a heating pad
- do not apply to wounds or damaged skin

Stop use and ask doctor if

- condition worsens
- symptoms persist for more than 7 days or clear up and occur again within a few days
- excessive skin irritation or redness occurs

If pregnant or breast-feeding, ask a health professional before use.

DIRECTIONS

- For use on adults and children over 12 years of age and older: Apply product on affected area, not more than 4 times daily
- children under 12 years of age: ask a doctor

INACTIVE INGREDIENTS

Denatured alcohol, Water, Peppermint oil, Glycerin, Polyacrylate Crosspolymer-6, MSM, Ilex paraguariensis leaf extract, Glucosamine sulphate, Chondroitin sulphate, Folic acid, Vitamin C, Vitamin D.

Keep out of reach of children to avoid accidental ingestion. If swallowed, get medical help or contact a Poison Control Center immediately.